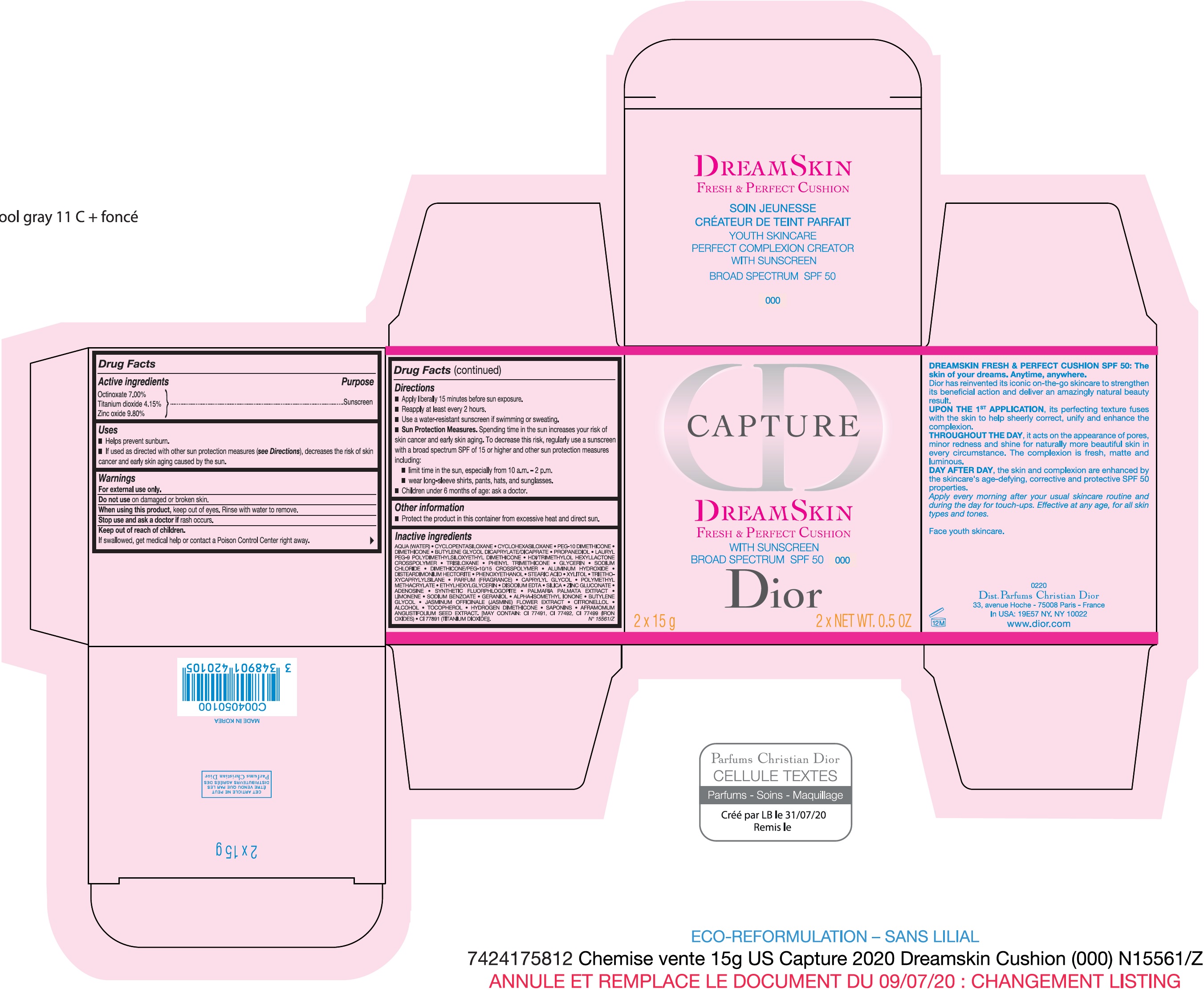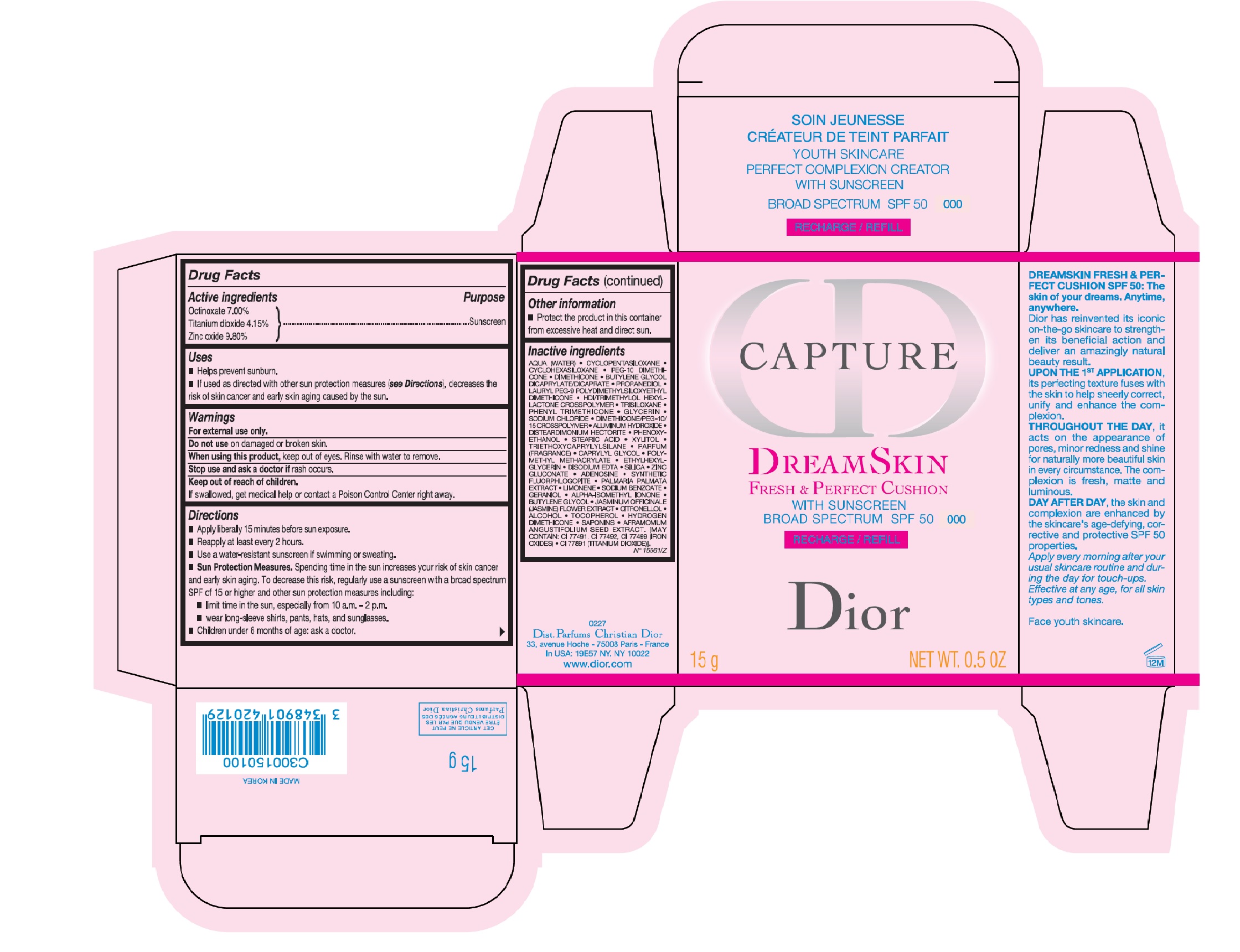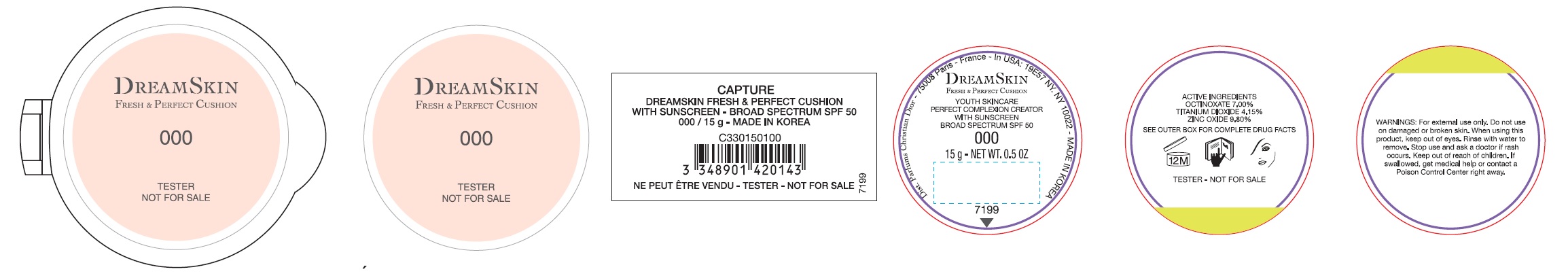 DRUG LABEL: CAPTURE DREAMSKIN FRESH and PERFECT CUSHION WITH SUNSCREEN BROAD SPECTRUM SPF 50 000
NDC: 61957-2303 | Form: EMULSION
Manufacturer: Parfums Christian Dior
Category: otc | Type: HUMAN OTC DRUG LABEL
Date: 20231103

ACTIVE INGREDIENTS: OCTINOXATE 0.07 mg/1 g; TITANIUM DIOXIDE 0.0415 mg/1 g; ZINC OXIDE 0.098 mg/1 g
INACTIVE INGREDIENTS: WATER; CYCLOMETHICONE 5; CYCLOMETHICONE 6; PEG-10 DIMETHICONE (600 CST); DIMETHICONE; BUTYLENE GLYCOL; PROPANEDIOL; LAURYL PEG-9 POLYDIMETHYLSILOXYETHYL DIMETHICONE; HEXAMETHYLENE DIISOCYANATE/TRIMETHYLOL HEXYLLACTONE CROSSPOLYMER; TRISILOXANE; PHENYL TRIMETHICONE; POLY(METHYL METHACRYLATE; 450000 MW); GLYCERIN; SODIUM CHLORIDE; DIMETHICONE/PEG-10/15 CROSSPOLYMER; ALUMINUM HYDROXIDE; DISTEARDIMONIUM HECTORITE; PHENOXYETHANOL; STEARIC ACID; XYLITOL; TRIETHOXYCAPRYLYLSILANE; CAPRYLYL GLYCOL; ETHYLHEXYLGLYCERIN; EDETATE DISODIUM ANHYDROUS; SILICON DIOXIDE; ADENOSINE; PALMARIA PALMATA; LIMONENE, (+)-; SODIUM BENZOATE; GERANIOL; ISOMETHYL-.ALPHA.-IONONE; JASMINUM OFFICINALE FLOWER; .BETA.-CITRONELLOL, (R)-; ALCOHOL; TOCOPHEROL; AFRAMOMUM ANGUSTIFOLIUM SEED; FERRIC OXIDE RED

CAPTURE DREAMSKIN FRESH & PERFECT CUSHION WITH SUNSCREEN BROAD SPECTRUM SPF 50 000

Active Ingredients

Octinoxate 7.00%

Titanium dioxide 4.15%

Zinc oxide 9.80%

Purpose

Antiseptic

Uses

- Helps prevent sunburn.
- If used as directed with other sun protection measures (), decreases the risk of skin cancer and early skin aging caused by the Sun. see Directions

Warnings

For external use only.

Do not use

on damaged or broken skin.

When using this product,

keep out of eyes. Rinse with water to remove.

Stop use and ask a doctor

if rash occurs.

Keep out of reach of children.

If swallowed, get medical help or contact a Poison Contral Center right away.

Directions

- Apply liberally 15 minutes before sun exposure.
- Reapply at least every 2 hours
- Use a water resistant sunscreen if swimming or sweating

- limit time in the sun, especially from 10 a.m. - 2 p.m.
- wear long-sleeve shirts, pants, hats, and sunglasses.
- Children under 6 months of age: ask a doctor.

. Spending time in the sun increases your risk of skin cancer and early skin aging. To decrease this risk, regularly use a sunscreen with a broad spectrum SPF of 15 or higher and other sun protection measures Sun Protection Measures

including:

Other information

- Protect the product in this container from excessive heat and direct sun.

Inactive ingredients:

AQUA (WATER)• CYCLOPENTASILOXANE• CYCLOHEXASILOXANE• PEG-10 DIMETHICONE•DIMETHICONE •BUTYLENE GLYCOL DICAPRYLATE/DICAPRATE• PROPANEDIOL •LAURYLPEG-9 POLYDIMETHYLSILOXYETHYL DIMETHICONE• HDVTRIMETHYLOL HEXYLLACTONE CROSSPOLYMER TRISILOXANE •PHENYL TRIMETHICONE• POLYMETHYL METHACRYLATE•GLYCERIN •SODIUM CHLORIDE• DIMETHICONE/PEG-10/15 CROSSPOLYMER •ALUMINUM HYDROXDE• DISTEARDIMONIUM HECTORITE •PHENOXYETHANOL •STEARIC ACID• XYLITOL •TRIETHOXYCAPRYLYLSILANE• PARFUM (FRAGRANCE) •CAPRYLYL GLYCOL•ETHYLHEXYLGLYCERIN •DISODIUM EDTA •SILICA •ZINC GLUCONATE• ADENOSINE•SYNTHETNC FLUORPHLOGOPITE •PALMARIA PALMAIA EXTRACT•LIMONENE•SODIUMBENZOATE•GERANIOL •ALPHA-ISOMETHYL IONONE• BUTYLENE GLYCOL• JASMINUM OFFICINALE (JASMINE) FLOWER EXTRACT• CITRONELLOL• ALCOHOL• TOCOPHEROL• HYDROGEN DIMETHICONE•SAPONINS• AFRAMOMUM ANGUSTIFOLIUM SEED EXTRACT.[MAY CONTAIN: CI 77491, CI77492, CI 77499 (IRON OXIDES) •CI 77891 (TITANIUM DIOXIDE)].